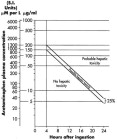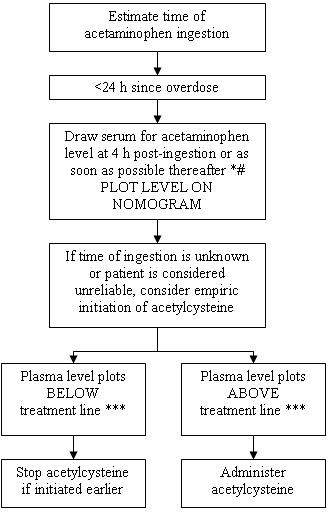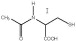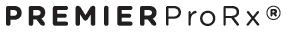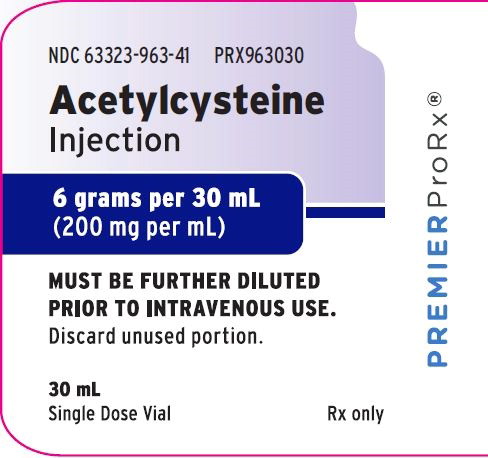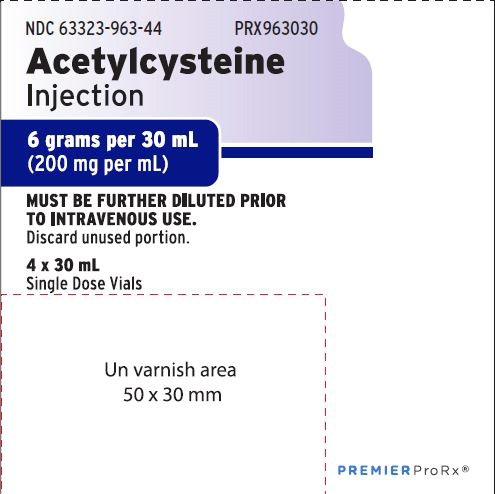 DRUG LABEL: Acetylcysteine
NDC: 63323-963 | Form: INJECTION, SOLUTION
Manufacturer: Fresenius Kabi USA, LLC
Category: prescription | Type: HUMAN PRESCRIPTION DRUG LABEL
Date: 20221031

ACTIVE INGREDIENTS: ACETYLCYSTEINE 200 mg/1 mL
INACTIVE INGREDIENTS: EDETATE DISODIUM 0.5 mg/1 mL; SODIUM HYDROXIDE; WATER

HIGHLIGHTS OF PRESCRIBING INFORMATION

These highlights do not include all the information needed to use ACETYLCYSTEINE INJECTION safely and effectively. See full prescribing information for ACETYLCYSTEINE INJECTION.
ACETYLCYSTEINE injection
Initial U.S. Approval: 2004.

1 INDICATIONS AND USAGE

Acetylcysteine Injection is an antidote for acetaminophen overdose indicated to prevent or lessen hepatic injury after ingestion of a potentially hepatotoxic quantity of acetaminophen (1)

2 DOSAGE AND ADMINISTRATION

The total dose of Acetylcysteine Injection is 300 mg/kg given as 3 separate doses and administered over a total of 21 hrs. Please refer to the guidelines below for dose preparation based upon patient weight.

Dosing for patients who weigh 5 kg to 20 kg (2.1):

Loading Dose: 150 mg/kg diluted in 3 mL/kg of diluent* administered over 1 hr

Second Dose: 50 mg/kg diluted in 7 mL/kg of diluent* administered over 4 hrs

Third Dose: 100 mg/kg diluted in 14 mL/kg of diluent* administered over 16 hrs

Dosing for patients who weigh 21 kg to 40 kg (2.1):

Loading Dose: 150 mg/kg diluted in 100 mL of diluent* administered over 1 hr

Second Dose: 50 mg/kg diluted in 250 mL of diluent* administered over 4 hrs

Third Dose: 100 mg/kg diluted in 500 mL of diluent* administered over 16 hrs

Dosing for patients who weigh 41 kg to 100 kg (2.1):

Loading Dose: 150 mg/kg diluted in 200 mL of diluent* administered over 1 hr

Second Dose: 50 mg/kg diluted in 500mL of diluent* administered over 4 hrs

Third Dose: 100 mg/kg diluted in 1,000 mL of diluent* administered over 16 hrs

* Acetylcysteine Injection is compatible with the following diluents; 5% Dextrose in Water, 0.45% Sodium Chloride Injection, and Sterile Water for Injection

Dosing for patients who weigh more than 100 kg (2.1):

No specific studies have been conducted to evaluate the use of or necessity of dosing adjustments in patients weighing over 100 kg. Limited information is available regarding the dosing requirements of patients that weigh more than 100 kg. The dose of Acetylcysteine Injection recommended in these patients should be a loading dose of 15,000 mg infused over one hour followed by a first maintenance dose of 5,000 mg over 4 hrs and a second maintenance dose of 10,000 mg over 16 hrs.

3 DOSAGE FORMS AND STRENGTHS

Each single dose vial contains 6 g/30 mL (200 mg/mL), Acetylcysteine Injection (3)

4 CONTRAINDICATIONS

Patients with previous anaphylactoid reaction to acetylcysteine (4)

5 WARNINGS AND PRECAUTIONS

- Monitor as acute flushing and erythema of the skin may occur; usually associated with the loading dose; often resolves spontaneously despite continued infusion (5.1)
- Monitor for serious anaphylactoid reactions; infusion may be interrupted until treatment of anaphylactoid symptoms has been initiated (5.1)
- Should be used with caution in patients with asthma, or where there is a history of bronchospasm (5.2)
- Total volume administered should be adjusted for patients less than 40 kg and for those requiring fluid restriction (5.3)

6 ADVERSE REACTIONS

Most common adverse reactions (incidence >2%) are rash, urticaria/facial flushing and pruritus 6.1)

To report SUSPECTED ADVERSE REACTIONS, contact Fresenius Kabi USA, LLC at 1-800-551-7176 or FDA at 1-800-FDA-1088 or www.fda.gov/medwatch.

7 DRUG INTERACTIONS

No drug-drug interaction studies have been conducted (7)

8 USE IN SPECIFIC POPULATIONS

Pregnancy: This drug should be used during pregnancy only if clearly needed (8.1)

Nursing Mothers: Unknown if drug is excreted in human milk (8.3)

Pediatric Use: See dose adjustment for patients < 40 kg (2)

FULL PRESCRIBING INFORMATION

1 INDICATIONS AND USAGE

Acetylcysteine Injection is an antidote for acetaminophen overdose indicated to prevent or lessen hepatic injury after ingestion of a potentially hepatotoxic quantity of acetaminophen. Overdose incidences are divided into two types; Acute Ingestion or Repeated Supratherapeutic Ingestion (RSI). [see Dosage and Administration (2) and Acetaminophen Assays – Interpretation and Methodology -(Acute or Repeated Supratherapeutic Ingestion) (1.1, 1.2)].
On admission for suspected acetaminophen overdose, a serum blood sample should be drawn at least 4 hours after ingestion to determine the acetaminophen level and will serve as a basis for determining the need for treatment with acetylcysteine. If the patient presents after 4 hours post-ingestion, the serum acetaminophen sample should be determined immediately.

Acetylcysteine Injection should be administered within 8 hours from acetaminophen ingestion for maximal protection against hepatic injury for patients whose serum acetaminophen levels fall above the "possible" toxicity line on the Rumack-Matthew nomogram (line connecting 150 mcg/mL at 4 hours with 37.5 mcg/mL at 12 hours); [see Acetaminophen Assays – Interpretation and Methodology (1.1, 1.2)] . If the time of ingestion is unknown, or the serum acetaminophen level is not available, cannot be interpreted, or is not available within the 8 hour time interval from acetaminophen ingestion, Acetylcysteine Injection should be administered immediately if 24 hours or less have elapsed from the reported time of ingestion of an overdose of acetaminophen, regardless of the quantity reported to have been ingested.

The aspartate aminotransferase (AST, SGOT), alanine aminotranferase (ALT, SGPT), bilirubin, prothrombin time, creatinine, blood urea nitrogen (BUN), blood glucose, and electrolytes also should be determined in order to monitor hepatic and renal function and electrolyte and fluid balance.

NOTE: The critical ingestion-treatment interval for maximal protection against severe hepatic injury is between 0 to 8 hours. Efficacy diminishes progressively after 8 hours and treatment initiation between 15 and 24 hours post-ingestion of acetaminophen yields limited efficacy. However, it does not appear to worsen the condition of patients and it should not be withheld, since the reported time of ingestion may not be correct.

1.1 Acetaminophen Assays Interpretation and Methodology – Acute Ingestion

The acute ingestion of acetaminophen in quantities of 150 mg/kg or greater may result in hepatic toxicity. However, the reported history of the quantity of a drug ingested as an overdose is often inaccurate and is not a reliable guide to therapy of the overdose. Therefore, plasma or serum acetaminophen concentrations, determined as early as possible, but no sooner than four hours following an acute overdose, are essential in assessing the potential risk of hepatotoxicity. If an assay for acetaminophen cannot be obtained, it is necessary to assume that the overdose is potentially toxic.

Interpretation of Acetaminophen Assays

1. When results of the plasma acetaminophen assay are available, refer to the nomogram in Figure 1 to determine if plasma concentration is in the potentially toxic range. Values above the line connecting 200 mcg/mL at 4 hours with 50 mcg/mL at 12 hours (probable line) are associated with a probability of hepatic toxicity if an antidote is not administered.
2. If the predetoxification plasma level is above the line connecting 150 mcg/mL at 4 hours with 37.5 mcg/mL at 12 hours (possible line), continue with maintenance doses of acetylcysteine. It is better to err on the safe side and thus this line, defining possible toxicity, is plotted 25% below the line defining probable toxicity.
3. If the predetoxification plasma level is below the line connecting 150 mcg/mL at 4 hours with 37.5 mcg/mL at 12 hours (possible line), there is minimal risk of hepatic toxicity, and Acetylcysteine treatment may be discontinued.

Estimating Potential for Hepatotoxicity: The following depiction of the Rumack- Matthew nomogram has been developed to estimate the probability that plasma levels in relation to intervals post-ingestion will result in hepatotoxicity.

The Rumack-Matthew nomogram may underestimate the risk for hepatotoxicity in some patients with risk factors such as chronic alcoholism, malnutrition, or CYP2E1 enzyme inducing drugs (e.g., isoniazid).

Figure 1. Rumack-Matthew Nomogram:

Figure 1. Michael J Hodgman, Alexander R Garrard, A Review of Acetaminophen Poisoning. Crit Care Clin. 28 (2012) 499-516. Stephen J. Wolf, Kennon Heard, et.al, Clinical Policy: Critical Issues in the Management of Patients Presenting to the Emergency Department with Acetaminophen Overdose. Ann Emerg Med. 2007:50:292-313.

1.2 Acetaminophen Assays Interpretation and Methodology – Repeated Supratherapeutic Ingestion

Repeated Supratherapeutic Ingestion (RSI) is defined as ingestion of acetaminophen at doses higher than those recommended for extended periods of time. The nomogram does not apply to patients with RSI. Treatment is based on the acetaminophen and elevated AST/ALT levels indicative of potential toxicity due to acetaminophen. For specific treatment information regarding the clinical management of repeated supratherapeutic acetaminophen overdose, please contact your regional poison center at 1-800-222-1222, or alternatively, a special health professional assistance line for acetaminophen overdose at 1-800-525-6115.

Figure 2. Acetylcysteine Injection Treatment Flow Chart

^1Acetaminophen levels drawn less than 4 hours post-ingestion may be misleading.

^2With an extended-release preparation, an acetaminophen level drawn less than 8 hours post-ingestion may be misleading. Draw a second level at 4 to 6 hours after the initial level. If either falls above the toxicity line, acetylcysteine treatment should be initiated.

^3Acetylcysteine may be withheld until acetaminophen assay results are available as long as initiation of treatment is not delayed beyond 8 hours post-ingestion. If more than 8 hours post-ingestion, start acetylcysteine treatment immediately.

2 DOSAGE AND ADMINISTRATION

The total dose of Acetylcysteine Injection is 300 mg/kg given as 3 separate doses and administered over a total of 21 hours. Please refer to the guidelines below for dose preparation based upon patient weight. The total volume administered should be adjusted for patients less than 40 kg and for those requiring fluid restriction (see Tables 1 and 2).

2.1 Administration Instructions (Three-Bag Method: Loading, Second and Third Dose)

Dosing for Patients who weigh 5 kg to 20 kg (Table 1):

Loading Dose: 150 mg/kg diluted in 3 mL/kg of diluent* administered over 1 hr

Second Dose: 50 mg/kg diluted in 7 mL/kg of diluent* administered over 4 hrs

Third Dose: 100 mg/kg diluted in 14 mL/kg of diluent* administered over 16 hrs

Table 1. Three Bag Method Dosage Guide by Weight in Patients 5 kg to 20 kg
Body Weight (kg) | Bag 1 (loading dose): 150 mg/kg in 3 mL/kg of diluent [Acetylcysteine Injection is compatible with the following diluents; 5% Dextrose in Water, 0.45% Sodium Chloride Injection, and Sterile Water for Injection.] infused over 1 hour |  | Bag 2 (second dose): 50 mg/kg in 7mL/kg of diluent infused over 4 hours |  | Bag 3 (third dose): 100 mg/kg diluted in 14 mL/kg of diluent infused over 16 hours
Body Weight (kg) | Acetylcysteine Injection Total Dose | Diluent volume | Acetylcysteine Injection Total Dose | Diluent volume | Acetylcysteine Injection Total Dose | Diluent volume
5 kg | 750 mg | 15 mL | 250 mg | 35 mL | 500 mg | 70 mL
10 kg | 1,500 mg | 30 mL | 500 mg | 70 mL | 1,000 mg | 140 mL
15 kg | 2,250 mg | 45 mL | 750 mg | 105 mL | 1,500 mg | 210 mL
20 kg | 3,000 mg | 60 mL | 1,000 mg | 140 mL | 2,000 mg | 280 mL

See also Section 2.2 Volume Adjustment: Patients less than 40 kg and Requiring Fluid Restriction

Dosing for patients who weigh 21 kg to 40 kg (Table 2):

Loading Dose: 150 mg/kg diluted in 100 mL of diluent* administered over 1 hr

Second Dose: 50 mg/kg diluted in 250 mL of diluent* administered over 4 hrs

Third Dose: : 100 mg/kg diluted in 500 mL of diluent* administered over 16 hrs

Table 2. Three Bag Method Dosage Guide by Weight in Patients 21 kg to 40 kg
Body Weight (kg) | Bag 1 (loading dose): 150 mg/kg in 100 mL of diluent [Acetylcysteine Injection is compatible with the following diluents; 5% Dextrose in Water 0.45% Sodium Chloride Injection, and Sterile Water for Injection.] infused over 1 hr | Bag 2 (second dose): 50 mg/kg in 250 mL of diluent infused over 4 hrs | Bag 3 (third dose): 100 mg/kg in 500 mL of diluent infused over 16 hrs
Body Weight (kg) | Acetylcysteine Injection Total Dose | Acetylcysteine Injection Total Dose | Acetylcysteine Injection Total Dose
21 kg | 3,150 mg | 1,050 mg | 2,100 mg
30 kg | 4,500 mg | 1,500 mg | 3,000 mg
40 kg | 6,000 mg | 2,000 mg | 4,000 mg

See also Section 2.2 Volume Adjustment: Patients less than 40 kg and Requiring Fluid Restriction.

Dosing for patients who weigh 41 kg to 100 kg (Table 3):

Loading Dose: 150 mg/kg diluted in 200 mL of diluent* administered over 1 hr

Second Dose: 50 mg/kg diluted in 500 mL of diluent* administered over 4 hrs

Third Dose: 100 mg/kg diluted in 1,000 mL of diluent administered over 16 hrs

Table 3. Three Bag Method Dosage Guide by Weight in Patients 41 kg to 100 kg
Body Weight (kg) | Bag 1 (loading dose): 150 mg/kg diluted in 200 mL of diluent [Acetylcysteine Injection is compatible with the following diluents; 5% Dextrose 0.45% Sodium Chloride Injection, and Sterile Water for Injection.] infused over 1 hr | Bag 2 (second dose): 50 mg/kg diluted in 500 mL of diluent infused over 4 hrs | Bag 3 (third dose): 100 mg/kg diluted in 1,000 mL of diluent infused over 16 hrs
Body Weight (kg) | Acetylcysteine Injection Total Dose | Acetylcysteine Injection Total Dose | Acetylcysteine Injection Total Dose
41 kg | 6,150 mg | 2,050 mg | 4,100 mg
50 kg | 7,500 mg | 2,500 mg | 5,000 mg
60 kg | 9,000 mg | 3,000 mg | 6,000 mg
70 kg | 10,500 mg | 3,500 mg | 7,000 mg
80 kg | 12,000 mg | 4,000 mg | 8,000 mg
90 kg | 13,500 mg | 4,500 mg | 9,000 mg
100 kg | 15,000 mg | 5,000 mg | 10,000 mg

Patients Weighing More Than 100 kg

No specific studies have been conducted to evaluate the use of or necessity of dosing adjustments in patients weighing over 100 kg. Limited information is available regarding the dosing requirements of patients that weigh more than 100 kg. The dose of Acetylcysteine Injection recommended in these patients should be a loading dose of 15,000 mg infused over a period of one hour followed by a first maintenance dose of 5,000 mg over 4 hours and a second maintenance dose of 10,000 mg over 16 hours (Table 3).

Continued Therapy beyond 21 Hours

While there is no clinical trial data to support infusions beyond 21 hours there is literature that supports continued infusion of acetylcysteine in some rare instances. In cases of suspected massive overdose, or with concomitant ingestion of other substances, or in patients with preexisting liver disease, the absorption and/or the half-life of acetaminophen may be prolonged, in such cases consideration should be given to the need for continued infusion of N-acetylcysteine beyond 21 hours. Acetaminophen levels and ALT/AST & INR should be checked before the end of the 21-hour infusion. If acetaminophen levels are still detectable, or in cases in which the ALT/AST are still increasing or the INR remains elevated, the infusion should be continued, and the treating physician should contact a US regional poison center at 1-800-222-1222, or alternatively, a “special health professional assistance line for acetaminophen overdose” at 1-800-525-6115 for assistance with dosing recommendations.

2.2 Volume Adjustment: Patients less than 40 kg and Requiring Fluid Restriction

The total volume administered should be adjusted for patients less than 40 kg and for those requiring fluid restriction. To avoid fluid overload, the volume of diluent should be reduced as clinically needed. If the volume of the infusion is not adjusted, fluid overload can occur, potentially resulting in hyponatremia, seizure and death. [ see Dosage and Administration (2)]

As Acetylcysteine Injection is hyperosmolar (2600 mOsmol/L), caution is advised when the diluent volume is decreased as the hyperosmolarity of the solution is increased. See Table 4 below for examples.

Table 4. Acetylcysteine Injection Concentration and Osmolarity
Acetylcysteine Injection Concentration (mg/mL) | Osmolarity in ½ Normal Saline | Osmolarity in D5W | Osmolarity in Sterile Water for Injection
7 mg/mL | 245 mOsmol/L | 343 mOsmol/L | 91 mOsmol/L [Osmolarity should be adjusted to a physiologically safe level, (generally not less than 150mOsmol/L in children).]
24 mg/m/L | 466 mOsmol/L | 564 mOsmol/L | 312 mOsmol/L

Single dose vial, preservative-free, discard unused portion. If vial was previously opened, do not use for intravenous administration.

Stability studies indicate that the diluted solution is stable for 24 hours at controlled room temperature.

Note: The color of Acetylcysteine Injection may turn from essentially colorless to a slight pink or purple once the stopper is punctured. The color change does not affect the quality of the product.

2.3 Renal Impairment

No data are available to determine if a dose adjustment in patients with moderate or severe renal impairment is required.

2.4 Hepatic Impairment

Although there was a threefold increase in acetylcysteine plasma concentrations in patients with hepatic cirrhosis, no data are available to determine if a dose adjustment in these patients is required. The published medical literature does not indicate that the dose of acetylcysteine in patients with hepatic impairment should be reduced.

3 DOSAGE FORMS AND STRENGTHS

Each single dose vial contains 6g/30mL (200 mg/mL) of Acetylcysteine. Acetylcysteine Injection is sterile and can be used for intravenous administration.

4 CONTRAINDICATIONS

Acetylcysteine Injection is contraindicated in patients with previous anaphylactoid reactions to acetylcysteine.

5 WARNINGS AND PRECAUTIONS

5.1 Anaphylactoid Reactions

Serious anaphylactoid reactions, including death in a patient with asthma, have been reported in patients administered acetylcysteine intravenously.
Acute flushing and erythema of the skin may occur in patients receiving acetylcysteine intravenously. These reactions usually occur 30 to 60 minutes after initiating the infusion and often resolve spontaneously despite continued infusion of acetylcysteine. Anaphylactoid reactions (defined as the occurrence of an acute hypersensitivity reaction during acetylcysteine administration including rash, hypotension, wheezing, and/or shortness of breath) have been observed in patients receiving intravenous acetylcysteine for acetaminophen overdose and occurred soon after initiation of the infusion [see Adverse Reactions (6.1)]. If a reaction to acetylcysteine involves more than simply flushing and erythema of the skin, it should be treated as an anaphylactoid reaction. This usually entails administering antihistaminic drugs and in severe cases may require administration of epinephrine. In addition, the acetylcysteine infusion may be interrupted until treatment of the anaphylactoid symptoms has been initiated and then carefully restarted. If the anaphylactoid reaction returns upon reinitiation of treatment or increases in severity, intravenous acetylcysteine should be discontinued and alternative patient management should be considered.

5.2 Monitoring Patients with Asthma

Acetylcysteine Injection should be used with caution in patients with asthma, or where there is a history of bronchospasm.

5.3 Volume Adjustment: Patients less than 40 kg and Requiring Fluid Restriction

The total volume administered should be adjusted for patients less than 40 kg and for those requiring fluid restriction. To avoid fluid overload, the volume of diluent should be reduced as needed [see Dosage and Administration (2)]. If volume is not adjusted fluid overload can occur, potentially resulting in hyponatremia, seizure and death.
For specific treatment information regarding the clinical management of acetaminophen overdose, please contact your regional poison center at 1-800-222-1222, or alternatively, a special health professional assistance line for acetaminophen overdose at 1-800-525-6115.

6 ADVERSE REACTIONS

6.1 Clinical Studies Experience

Because clinical trials are conducted under widely varying conditions, adverse reaction rates observed in the clinical trials of a drug cannot be directly compared to rates in the clinical trials of another drug and may not reflect the rates observed in practice.

In the literature the most frequently reported adverse reactions attributed to intravenous acetylcysteine administration were rash, urticaria and pruritus. The frequency of adverse reactions has been reported to be between 0.2% and 20.8%, and they most commonly occur during the initial loading dose of acetylcysteine.

Loading Dose/Infusion Rate Study

The incidence of drug-related adverse reactions occurring within the first 2 hours following acetylcysteine administration reported in a randomized study in patients with acetaminophen poisoning is presented in Table 5 by preferred term. In this study patients were randomized to a 15-minute or a 60-minute loading dose regimen.

Within the first 2 hours following intravenous acetylcysteine administration, 17% developed an anaphylactoid reaction (18% in the 15-minute treatment group; 14% in the 60-minute treatment group) in this randomized, open-label, multi-center clinical study conducted in Australia to compare the rates of anaphylactoid reactions between two rates of infusion for the intravenous acetylcysteine loading dose [see Warnings (Section 5) and Clinical Studies - Loading Dose/Infusion Rate Study (Section 14) ].

Table 5. Incidence of Drug-Related Adverse Reactions Occurring Within the First 2 Hours Following Study Drug Administration by Preferred Term: Loading Dose/Infusion Rate Study
Treatment Group | 15-min |  |  |  | 60-min
Number of Patients | n=109 |  |  |  | n=71
Cardiac disorders | 5 (5%) |  |  |  | 2 (3%)
Severity: Tachycardia NOS | Unkn | Mild | Moderate | Severe | Unkn | Mild | Moderate | Severe
Severity: Tachycardia NOS |  | 4 (4%) | 1 (1%) |  |  | 2 (3%)
Gastrointestinal disorders | 16 (15%) |  |  |  | 7 (10%)
Severity: Nausea Vomiting NOS | Unkn | Mild | Moderate | Severe | Unkn | Mild | Moderate | Severe
Severity: Nausea Vomiting NOS | 1(1%) |  | 6 (6%) |  |  | 1 (1%) | 1 (1%)
Severity: Nausea Vomiting NOS |  | 2 (2%) | 11 (10%) |  |  | 2 (3%) | 4 (6%)
Immune System Disorders | 20 (18%) |  |  |  | 10 (14%)
Severity: Anaphylactoid reaction | Unkn | Mild | Moderate | Severe | Unkn | Mild | Moderate | Severe
Severity: Anaphylactoid reaction | 2(2%) | 6 (6%) | 11 (10%) | 1 (1%) |  | 4 (6%) | 5 (7%) | 1 (1%)
Respiratory, thoracic and mediastinal disorders | 2 (2%) |  |  |  | 2 (3%)
Severity: Pharyngitis Rhinorrhoea Rhonchi Throat tightness | Unkn | Mild | Moderate | Severe | Unkn | Mild | Moderate | Severe
Severity: Pharyngitis Rhinorrhoea Rhonchi Throat tightness |  |  | 1 (1%)
Severity: Pharyngitis Rhinorrhoea Rhonchi Throat tightness |  | 1 (1%)
Severity: Pharyngitis Rhinorrhoea Rhonchi Throat tightness |  |  |  |  |  | 1 (1%)
Severity: Pharyngitis Rhinorrhoea Rhonchi Throat tightness |  |  |  |  |  | 1 (1%)
Skin & subcutaneous tissue disorders | 6 (6%) |  |  |  | 5 (7%)
Severity: Pruritus Rash NOS | Unkn | Mild | Moderate | Severe | Unkn | Mild | Moderate | Severe
Severity: Pruritus Rash NOS |  | 1 (1%) |  |  |  | 2 (3%)
Severity: Pruritus Rash NOS |  | 3 (3%) | 2 (2%) |  |  | 3 (4%)
Vascular disorders | 2 (2%) |  |  |  | 3 (4%)
Severity: Flushing | Unkn | Mild | Moderate | Severe | Unkn | Mild | Moderate | Severe
Severity: Flushing |  | 1 (1%) | 1 (1%) |  |  | 2 (3%) | 1 (1%)
Unkn=Unknown

Postmarketing Safety Study
A large multi-center study was performed in Canada where data were collected from patients who were treated with intravenous acetylcysteine for acetaminophen overdose between 1980 and 2005. This study evaluated 4709 adult cases and 1905 pediatric cases. The incidence of anaphylactoid reactions in adult (overall incidence 7.9%) and pediatric (overall incidence 9.5%) patients is presented in Tables 6 and 7.

Table 6.Distribution of reported reactions in adult patients receiving intravenous acetylcysteine
 | Incidence (%)
Reaction | % of Patients (n=4709)
Urticaria/Facial Flushing | 6.1%
Pruritus | 4.3%
Respiratory Symptoms [Respiratory symptoms are defined as presence of any of the following: cough, wheezing, stridor, shortness of breath, chest tightness, respiratory distress, or bronchospasm.] | 1.9%
Edema | 1.6%
Hypotension | 0.1%
Anaphylaxis | 0.1%

Table 7 Distribution of reported reactions in pediatric patients receiving intravenous acetylcysteine
 | Incidence (%)
Reaction | % of Patients (n=1905)
Urticaria/Facial Flushing | 7.6%
Pruritus | 4.1%
Respiratory Symptoms [Respiratory symptoms are defined as presence of any of the following: cough, wheezing, stridor, shortness of breath, chest tightness, respiratory distress, or bronchospasm.] | 2.2%
Edema | 1.2%
Anaphylaxis | 0.2%
Hypotension | 0.1%

7 DRUG INTERACTIONS

No drug-drug interaction studies have been conducted.

8 USE IN SPECIFIC POPULATIONS

8.1 Pregnancy

Pregnancy Category B

There are no adequate and well-controlled studies of Acetylcysteine Injection in pregnant women. However, limited case reports of pregnant women exposed to acetylcysteine during various trimesters did not report any adverse maternal, fetal or neonatal outcomes.

There are published reports on four pregnant women with acetaminophen toxicity, who were treated with oral or intravenous acetylcysteine at the time of delivery. Acetylcysteine crossed the placenta and was measurable following delivery in serum and cord blood of three viable infants and in cardiac blood of a fourth infant at autopsy (22 weeks gestational age who died 3 hours after birth). No adverse sequelae developed in the three viable infants. All mothers recovered and none of the infants had evidence of acetaminophen poisoning.

Reproduction studies were performed in rats at oral doses up to 2,000 mg/kg/day (1.1 times the recommended total human intravenous dose of 300 mg/kg based on body surface area comparison) and in rabbits at oral doses up to 1,000 mg/kg/day (1.1 times the recommended total human intravenous dose of 300 mg/kg based on body surface area comparison). No effects on fertility or harm to the fetus due to acetylcysteine were observed.

8.3 Nursing Mothers

It is not known whether Acetylcysteine Injection is present in human milk. Because many drugs are excreted in human milk, caution should be exercised when acetylcysteine is administered to a nursing woman. Based on the pharmacokinetics of acetylcysteine, it should be nearly completely cleared 30 hours after administration. Nursing women may consider resuming nursing 30 hours after administration.

8.4 Pediatric Use

No adverse effects were noted during intravenous infusion with acetylcysteine at a mean rate of 4.2 mg/kg/h for 24 hours to 10 preterm newborns ranging in gestational age from 25 to 31 weeks and in weight from 500 to 1380 grams in one study or in 6 newborns ranging in gestational age from 26 to 30 weeks and in weight from 520 to 1335 grams infused with acetylcysteine at 0.1 to 1.3 mg/kg/h for 6 days. Elimination of acetylcysteine was slower in these infants than in adults; mean elimination half-life was 11 hours. There are no adequate and well-controlled studies in pediatric patients.

8.5 Geriatric Use

The clinical studies do not provide a sufficient number of geriatric subjects to determine whether the elderly respond differently.

10 OVERDOSAGE

Single intravenous doses of acetylcysteine at 1000 mg/kg in mice, 2445 mg/kg in rats, 1500 mg/kg in guinea pigs, 1200 mg/kg in rabbits and 500 mg/kg in dogs were lethal. Symptoms of acute toxicity were ataxia, hypoactivity, labored respiration, cyanosis, loss of righting reflex and convulsions.

11 DESCRIPTION

Acetylcysteine injection is an intravenous antidote for the treatment of acetaminophen overdose. Acetylcysteine is the nonproprietary name for the N-acetyl derivative of the naturally occurring amino acid, L-cysteine (N-acetyl-L-cysteine, NAC). The compound is a white crystalline powder, which melts in the range of 104° to 110°C and has a very slight odor. The molecular formula of the compound is C5H9NO3S, and its molecular weight is 163.2. Acetylcysteine has the following structural formula:

Acetylcysteine Injection is supplied as a sterile solution in vials containing 20% w/v (200 mg/mL) acetylcysteine. The pH of the solution ranges from 6.0 to 7.5. Acetylcysteine Injection contains the following inactive ingredients: 0.5 mg/mL disodium edetate, sodium hydroxide (used for pH adjustment), and water for injection, USP.

12 CLINICAL PHARMACOLOGY

12.1 Mechanism of Action

Acetaminophen Overdose:

Acetaminophen is absorbed from the upper gastrointestinal tract with peak plasma levels occurring between 30 and 60 minutes after therapeutic doses and usually within 4 hours following an overdose. It is extensively metabolized in the liver to form principally the sulfate and glucoronide conjugates which are excreted in the urine. A small fraction of an ingested dose is metabolized in the liver by isozyme CYP2E1 of the cytochrome P-450 mixed function oxidase enzyme system to form a reactive, potentially toxic, intermediate metabolite. The toxic metabolite preferentially conjugates with hepatic glutathione to form nontoxic cysteine and mercapturic acid derivatives, which are then excreted by the kidney. Recommended therapeutic doses of acetaminophen are not believed to saturate the glucuronide and sulfate conjugation pathways and therefore are not expected to result in the formation of sufficient reactive metabolite to deplete glutathione stores. However, following ingestion of a large overdose, the glucuronide and sulfate conjugation pathways are saturated resulting in a larger fraction of the drug being metabolized via the cytochrome P-450 pathway and therefore, the amount of acetaminophen metabolized to the reactive intermediate increases. The increased formation of the reactive metabolite may deplete the hepatic stores of glutathione with subsequent binding of the metabolite to protein molecules within the hepatocyte resulting in cellular necrosis.
Acetylcysteine Intravenous Treatment:

Acetylcysteine has been shown to reduce the extent of liver injury following acetaminophen overdose. It is most effective when given early, with benefit seen principally in patients treated within 8-10 hours of the overdose. Acetylcysteine likely protects the liver by maintaining or restoring the glutathione levels, or by acting as an alternate substrate for conjugation with, and thus detoxification of, the reactive metabolite.

12.3 Pharmacokinetics

Distribution:

The steady-state volume of distribution (Vdss) and the protein binding for acetylcysteine were reported to be 0.47 liter/kg and 83%, respectively.

Metabolism:

Acetylcysteine may form cysteine, disulfides and conjugates in vivo (N, N'-diacetylcysteine, N-acetylcysteine-cysteine, N-acetylcysteine- glutathione, N-acetylcysteine-protein, etc). Based on published data, it was reported that after an oral dose of^35S-acetylcysteine, about 22% of total radioactivity was excreted in urine after 24 hours. No metabolites were identified.

Elimination:

After a single intravenous dose of acetylcysteine, the plasma concentration of total acetylcysteine declined in a poly-exponential decay manner with a mean terminal half-life (T1/2) of 5.6 hours. The mean clearance (CL) for acetylcysteine was reported to be 0.11 liter/hr/kg and renal CL constituted about 30% of total CL.

Special Populations:

Gender: Adequate information is not available to assess if there are differences in pharmacokinetics (PK) between males and females.

Pediatric: The mean elimination T1/2 of acetylcysteine is longer in newborns (11 hours) than in adults (5.6 hours). Pharmacokinetic information is not available in other age groups.

Pregnant Women: In four pregnant women with acetaminophen toxicity, oral or I.V. acetylcysteine was administered at the time of delivery. Acetylcysteine was detected in the cord blood of 3 viable infants and in cardiac blood of a fourth infant sampled at autopsy [see Pregnancy (8.1)].

Hepatic Impairment: In subjects with severe liver damage, i.e., cirrhosis due to alcohol (with Child-Pugh score of 7 to 13), or primary and/or secondary biliary cirrhosis (with Child-Pugh score of 5 to 7), mean T1/2 increased by 80% while mean CL decreased by 30% compared to the control group.

Renal Impairment: Pharmacokinetic information is not available in patients with renal impairment.

Geriatric Patients: Adequate information on acetylcysteine PK in geriatric patients is not available.

13 NONCLINICAL TOXICOLOGY

13.1 Carcinogenesis, Mutagenesis, Impairment of Fertility

Long-term studies in animals have not been performed to evaluate the carcinogenic potential of acetylcysteine.

Acetylcysteine was not genotoxic in the Ames test or the in vivo mouse micronucleus test. It was, however, positive in the in vitro mouse lymphoma cell (L5178Y/TK+/-) forward mutation test.

Treatment of male rats with acetylcysteine at an oral dose of 250 mg/kg/day for 15 weeks (0.1 times the recommended human dose of 300 mg/kg based on body surface comparison) did not affect the fertility or general reproductive performance.

14 CLINICAL STUDIES

Loading Dose/Infusion Rate Study

A randomized, open-label, multi-center clinical study was conducted in Australia to compare the rates of anaphylactoid reactions between two rates of infusion for the intravenous acetylcysteine loading dose. One hundred nine subjects were randomized to a 15 minute infusion rate and seventy-one subjects were randomized to a 60 minute infusion rate. The loading dose was 150 mg/kg followed by a maintenance dose of 50 mg/kg over 4 hours and then 100 mg/kg over 16 hours. Of the 180 patients, 27% were male and 73% were female. Ages ranged from 15 to 83 years, with the mean age being 29.9 years (±13.0).

A subgroup of 58 subjects (33 in the 15-minute treatment group; 25 in the 60-minute treatment group) was treated within 8 hours of acetaminophen ingestion. No hepatotoxicity occurred within this subgroup; however with 95% confidence, the true hepatotoxicity rates could range from 0% to 9% for the 15-minute treatment group and from 0% to 12% for the 60-minute treatment group.

Observational Study

An open-label, observational database contained information on 1,749 patients who sought treatment for acetaminophen overdose over a 16-year period. Of the 1,749 patients, 65% were female, 34% were male and less than 1% was transgender. Ages ranged from 2 months to 96 years, with 71.4% of the patients falling in the 16 to 40 year old age bracket. A total of 399 patients received acetylcysteine treatment. A post-hoc analysis identified 56 patients who (1) were at high or probable risk for hepatotoxicity (APAP greater than 150 mg/L at the four hours line according to the Australian nomogram) and (2) had a liver function test. Of the 53 patients who were treated with intravenous acetylcysteine (300 mg/kg intravenous acetylcysteine administered over 20 to 21 hours) within 8 hours, two (4%) developed hepatotoxicity (AST or ALT greater than 1,000 U/L). Twenty-one of 48 (44%) patients treated with acetylcysteine after 15 hours developed hepatotoxicity. The actual number of hepatotoxicity outcomes may be higher than what is reported here. For patients with multiple admissions for acetaminophen overdose, only the first overdose treated with intravenous acetylcysteine was examined. Hepatotoxicity may have occurred in subsequent admissions.

Evaluable data were available from a total of 148 pediatric patients (less than 16 years of age) who were admitted for poisoning following ingestion of acetaminophen, of whom 23 were treated with intravenous acetylcysteine. Of the 23 patients who received intravenous acetylcysteine treatment, 3 patients (13%) had an adverse reaction (anaphylactoid reaction, rash and flushing, transient erythema). There were no deaths of pediatric patients. None of the pediatric patients receiving intravenous acetylcysteine developed hepatotoxicity while two patients not receiving intravenous acetylcysteine developed hepatotoxicity. The number of pediatric patients is too small to provide a statistically significant finding of efficacy, however the results appear to be consistent to those observed for adults.

Postmarketing Safety Study [see 6.1 Clinical Studies Experience]

16 HOW SUPPLIED/STORAGE AND HANDLING

Acetylcysteine Injection is available as a 20% solution (200 mg/mL) in 30 mL single dose glass vials. Each single dose vial contains 6 g/30 mL (200 mg/mL) of Acetylcysteine. Acetylcysteine Injection is sterile and can be used for intravenous administration.

Acetylcysteine Injection is available as:

Product Code | Unit of Sale | Strength | Each
PRX963030 | NDC 63323-963-44; Unit of 4 | 20% (6 grams per 30 mL); (200 mg per mL) | NDC 63323-963-41; 30 mL Single Dose glass vial

Do not use previously opened vials for intravenous administration.

Note: The color of Acetylcysteine Injection may turn from essentially colorless to a slight pink or purple once the stopper is punctured. The color change does not affect the quality of the product.

The stopper in the Acetylcysteine Injection vial is formulated with a synthetic base-polymer and does not contain Natural Rubber Latex, Dry Natural Rubber, or blends of Natural Rubber.

Storage

Store unopened vials at controlled room temperature, 20° to 25°C (68° to 77°F) [see USP Controlled Room Temperature].

17 PATIENT COUNSELING INFORMATION

Sensitivity to acetylcysteine: Patients should be advised to report to their physician any history of sensitivity to acetylcysteine [see Contraindications (4)]

Asthma: Patients should be advised to report to their physician any history of asthma [see Warnings and Precautions (5)]

For all questions concerning adverse reactions associated with the use of this product or for Inquiries concerning our products, please contact us at 1-800-551-7176.

For specific treatment information regarding the clinical management of acetaminophen overdose, please contact your regional poison center at 1-800-222-1222, or alternatively, a special health professional assistance line for acetaminophen overdose at 1-800-525-6115.

PREMIERProRx® is a registered trademark of Premier Healthcare Alliance, L.P., used under license.

Manufactured for:

Fresenius Kabi

Lake Zurich, IL 60047
Made in India
www.fresenius-kabi.com/us
451618/Issued: February 2019

PACKAGE LABEL

PACKAGE LABEL - PRINCIPAL DISPLAY - Acetylcysteine 30 mL Single Dose Vial Label
NDC 63323-963-41

PRX963030
Acetylcysteine Injection
6 grams per 30 mL
(200 mg per mL)

MUST BE FURTHER DILUTED PRIOR TO INTRAVENOUS USE.
Discard unused portion.
30 mL
Single Dose Vial Rx only

PACKAGE LABEL

PACKAGE LABEL - PRINCIPAL DISPLAY - Acetylcysteine 30 mL Single Dose Vial Carton Panel

NDC 63323-963-44
PRX963030
Acetylcysteine Injection
6 grams per 30 mL
(200 mg per mL)

MUST BE FURTHER DILUTED PRIOR TO INTRAVENOUS USE.
Discard unused portion.
4 x 30 mL
Single Dose Vials

PREMIERProRx®